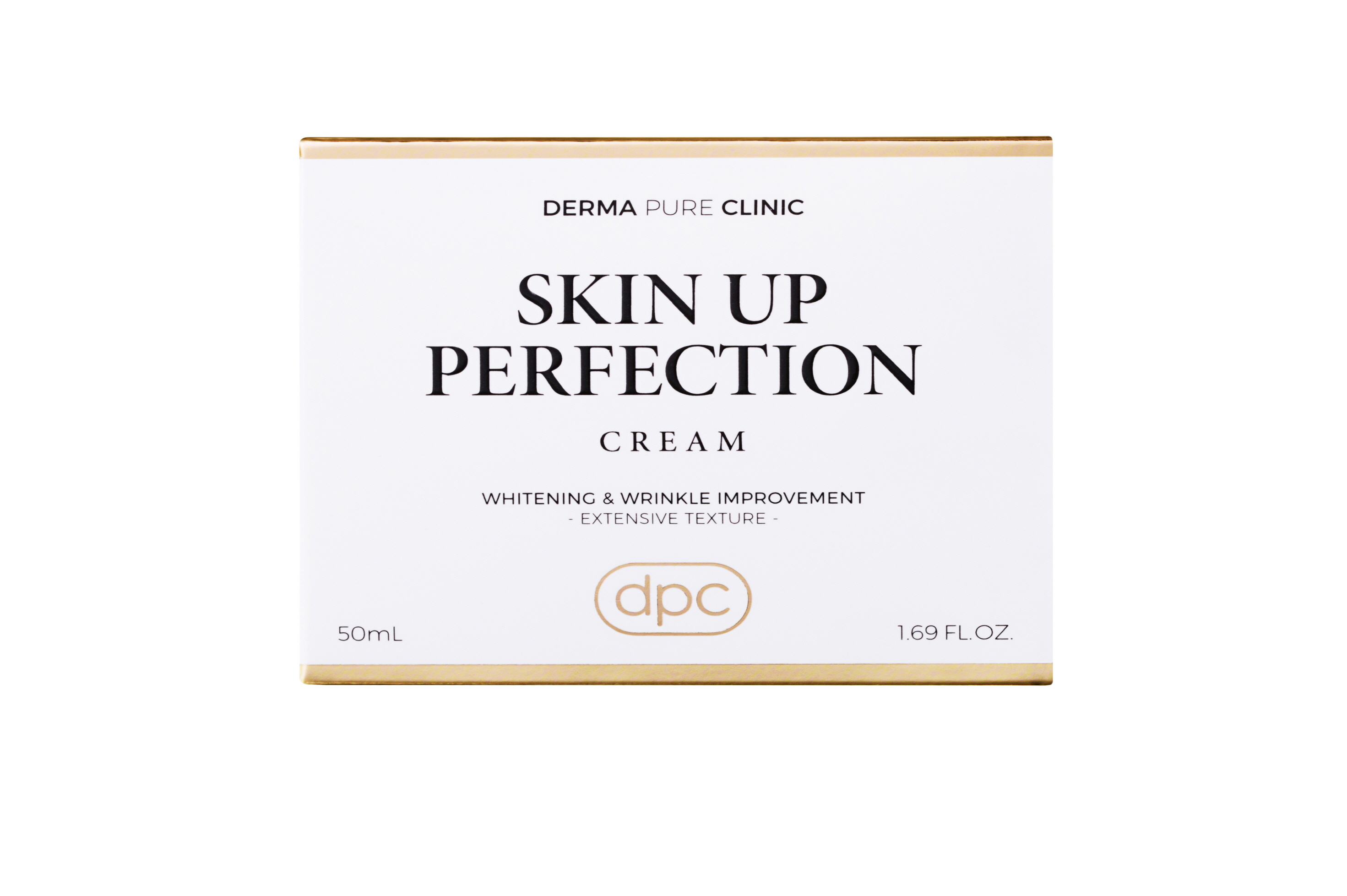 DRUG LABEL: DPC Skin Up Perfection
NDC: 71673-0006 | Form: CREAM
Manufacturer: MSCO
Category: otc | Type: HUMAN OTC DRUG LABEL
Date: 20170823

ACTIVE INGREDIENTS: ADENOSINE 0.04 g/100 mL; NIACINAMIDE 2 g/100 mL
INACTIVE INGREDIENTS: WATER; HYALURONATE SODIUM; GLYCERIN

Drug Facts

ACTIVE INGREDIENT

NIACINAMIDE, ADENOSINE

INACTIVE INGREDIENT

Water
Glycerin
Butylene Glycol
Cetyl Ethylhexanoate
Hydrogenated Poly(C6-14 Olefin)
Macadamia Integrifolia Seed Oil
Propanediol
Cyclopentasiloxane
Caprylic/Capric/Myristic/Stearic Triglyceride
Diisostearyl Malate
Behenyl Alcohol
Bis-Diglyceryl Polyacyladipate-2
Cetearyl Alcohol
Dimethicone
Glyceryl Stearate SE
Pentylene Glycol
Hydrogenated Polyisobutene
Polysorbate 60
Glyceryl Stearate
PEG-100 Stearate
Cyclohexasiloxane
Squalane
Phenoxyethanol
Caprylyl Glycol
Fragrance(Parfum)
Dimethicone/Vinyl Dimethicone Crosspolymer
Sodium Acrylate/Sodium Acryloyldimethyl Taurate Copolymer
Ammonium Acryloyldimethyltaurate/VP Copolymer
Tocopheryl Acetate
Xanthan Gum
Acrylates/C10-30 Alkyl Acrylate Crosspolymer
Tromethamine
Sea Cucumber Extract
Isohexadecane
Polysorbate 80
Caramel
Sorbitan Oleate
Ethyl Hexanediol
Anemarrhena Asphodeloides Root Extract
Yellow 6 (CI 15985)
Tocopherol
Hydrolyzed Extensin

PURPOSE

Anti wrinkle

Whitening

keep out of reach of the children

INDICATIONS AND USAGE

Apply a proper amount on the skin and spread evenly.

WARNINGS

For external use only.
Avoid contact with eyes. Not for human consumption.
Discontinue use if irritation occurs.
If irritation persists, consult a physician.

DOSAGE AND ADMINISTRATION

for external use only